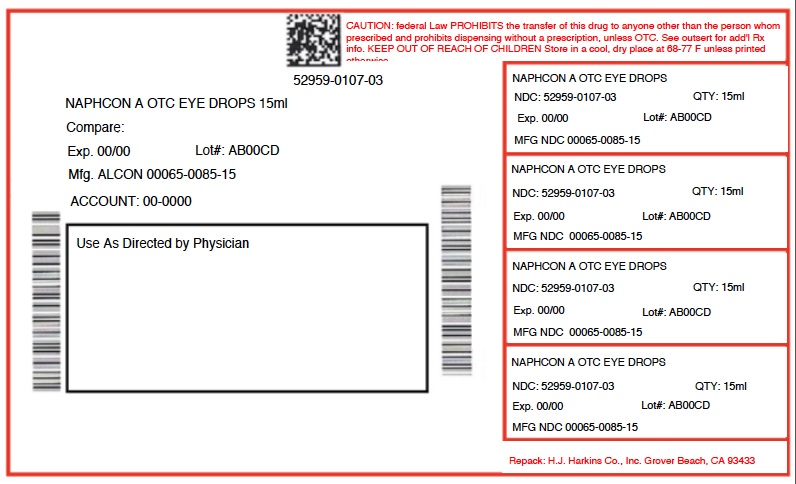 DRUG LABEL: NAPHCON A
NDC: 52959-107 | Form: SOLUTION/ DROPS
Manufacturer: H.J. Harkins Company, Inc.
Category: otc | Type: HUMAN OTC DRUG LABEL
Date: 20180821

ACTIVE INGREDIENTS: NAPHAZOLINE HYDROCHLORIDE 0.25 mg/1 mL; PHENIRAMINE MALEATE 3 mg/1 mL
INACTIVE INGREDIENTS: BENZALKONIUM CHLORIDE; WATER; SODIUM BORATE; SODIUM CHLORIDE; BORIC ACID; EDETATE DISODIUM; SODIUM HYDROXIDE; HYDROCHLORIC ACID

0107-03

WARNINGS

For external use only

DO NOT USE

- if you are sensitive to any ingredient in this product
- if this solution changes color or becomes cloudy

ASK DOCTOR

- narrow angle glaucoma
- heart disease
- high blood pressure
- trouble urinating

WHEN USING

- pupils may become enlarged temporarily causing light sensitivity
- overuse may cause more eye redness
- remove contact lenses before using
- to avoid contamination, do not touch tip of container to any surface
- replace cap after each use

STOP USE

- you feel eye pain
- changes in vision occur
- redness or irritation of the eye(s) gets worse or lasts more than 72 hours

KEEP OUT OF REACH OF CHILDREN

- If swallowed, get medical help or contact a Poison Control Center right away. Accidental swallowing by infants and children may lead to coma and marked reduction in body temperature.

DOSAGE AND ADMINISTRATION

- adults and children 6 years and over: put 1 or 2 drops in the affected eye(s) up to 4 times daily
- children under 6 years: ask a doctor

INACTIVE INGREDIENT

benzalkonium chloride, boric acid, edetate disodium, purified water, sodium borate, sodium chloride, sodium hydroxide and/or hydrochloric acid

INDICATIONS AND USAGE

for the temporary relief of redness and itching of the eye(s) due to:

- ragweed
- pollen
- grass
- animal dander and hair

PURPOSE

- Redness Reliever and Antihistamine Eye Drops
- Relieves Itching & Redness
- EYE ALLERGY RELIEF

ACTIVE INGREDIENT

Naphazoline HCl 0.025% and Pheniramine Maleate 0.3%